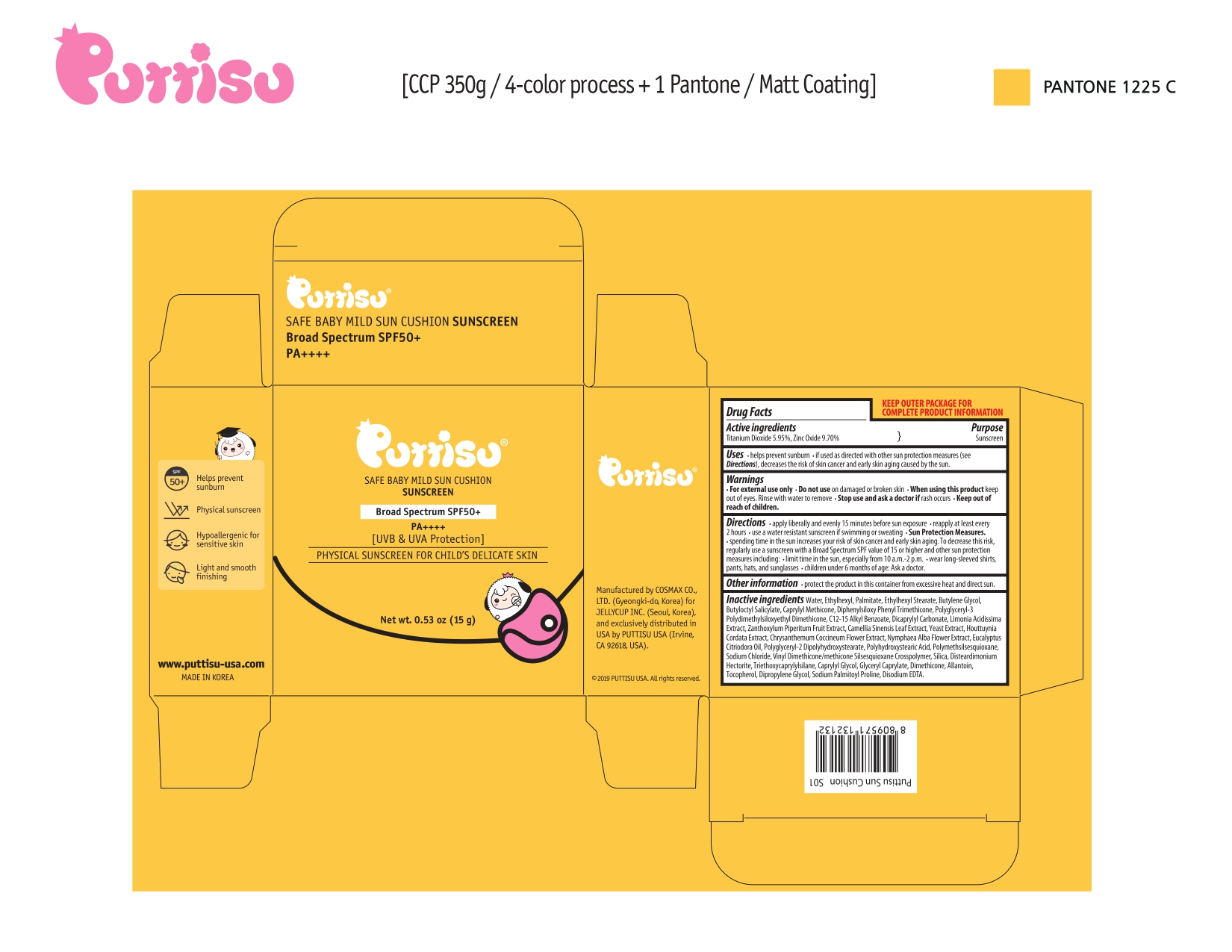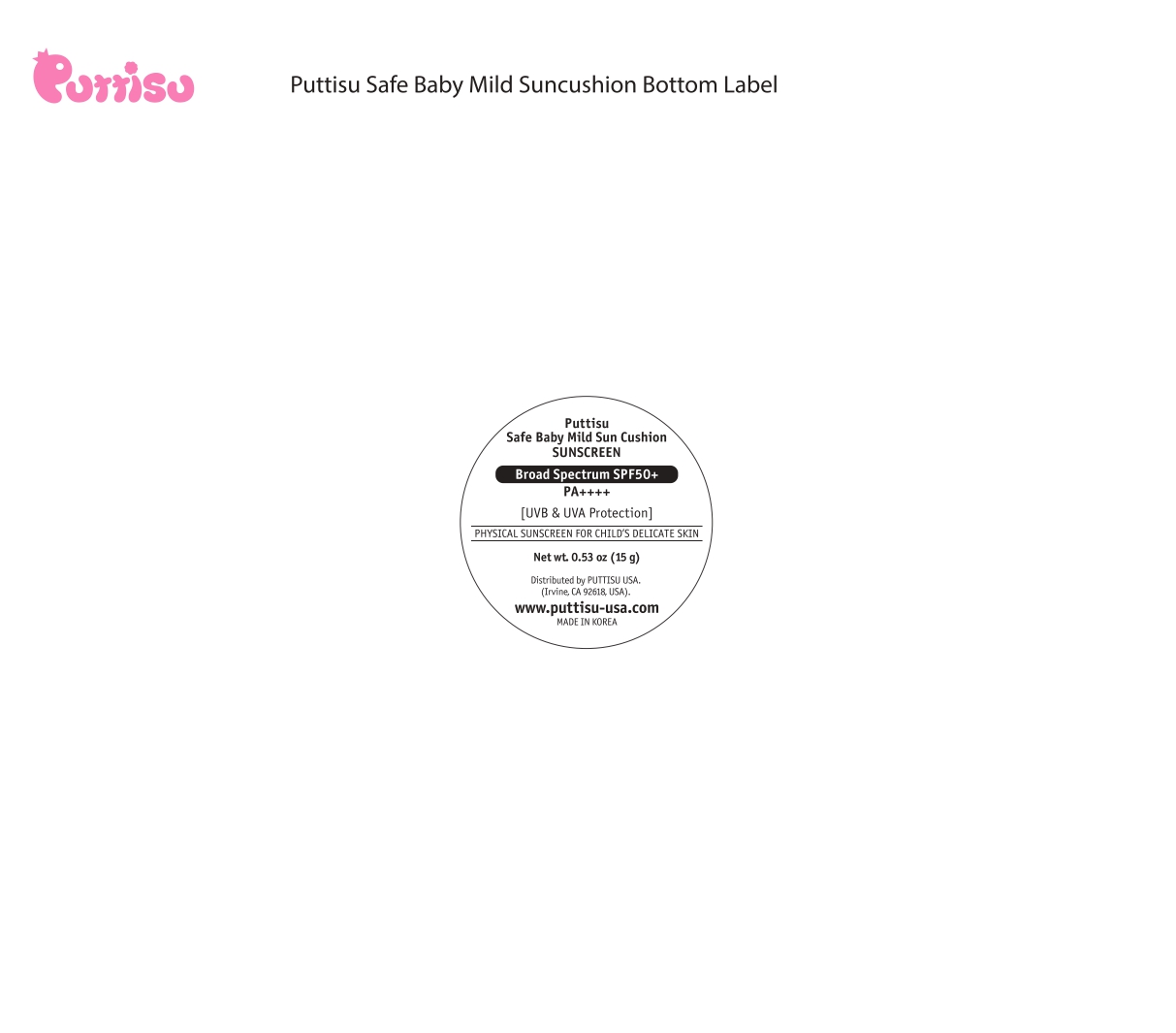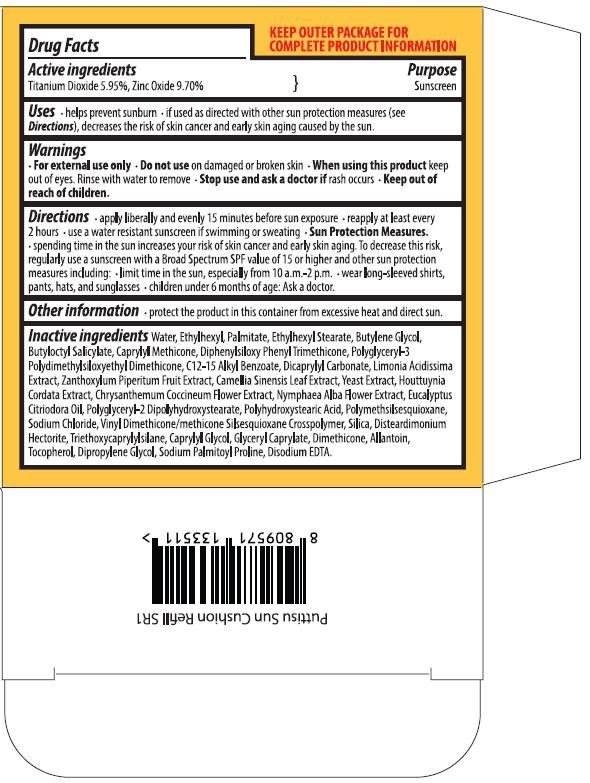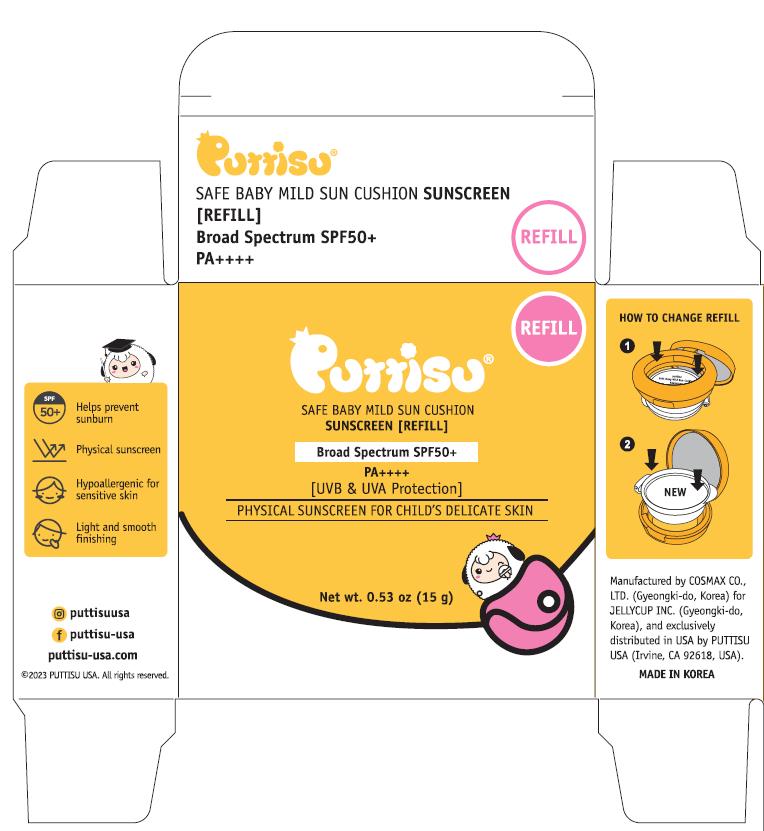 DRUG LABEL: Puttisu
NDC: 73419-0001 | Form: LIQUID
Manufacturer: Jellycup, Inc.
Category: otc | Type: HUMAN OTC DRUG LABEL
Date: 20241219

ACTIVE INGREDIENTS: ZINC OXIDE 5.95 g/100 mL; TITANIUM DIOXIDE 9.7 g/100 mL
INACTIVE INGREDIENTS: POLYHYDROXYSTEARIC ACID STEARATE; POLYMETHYLSILSESQUIOXANE (11 MICRONS); VINYL DIMETHICONE/METHICONE SILSESQUIOXANE CROSSPOLYMER; SILICON DIOXIDE; DICAPRYLYL CARBONATE; CAPRYLYL TRISILOXANE; DIPHENYLSILOXY PHENYL TRIMETHICONE; DIMETHICONE; DIPROPYLENE GLYCOL; GREEN TEA LEAF; YEAST, UNSPECIFIED; HOUTTUYNIA CORDATA TOP; TANACETUM COCCINEUM FLOWER; DISTEARDIMONIUM HECTORITE; TOCOPHEROL; LIMONIA ACIDISSIMA BARK; POLYGLYCERYL-3 POLYDIMETHYLSILOXYETHYL DIMETHICONE (4000 MPA.S); ALKYL (C12-15) BENZOATE; ZANTHOXYLUM PIPERITUM FRUIT PULP; CORYMBIA CITRIODORA LEAF OIL; POLYGLYCERYL-2 DIPOLYHYDROXYSTEARATE; ALLANTOIN; SODIUM PALMITOYL PROLINE; SODIUM CHLORIDE; TRIETHOXYCAPRYLYLSILANE; CAPRYLYL GLYCOL; GLYCERYL CAPRYLATE; DISODIUM EDTA-COPPER; WATER; ETHYLHEXYL PALMITATE; ETHYLHEXYL STEARATE; BUTYLENE GLYCOL; BUTYLOCTYL SALICYLATE

ACTIVE INGREDIENT

Titanium Dioxide 5.95%, Zinc Oxide 9.70%

PURPOSE

Sunscreen

INDICATIONS AND USAGE

- helps prevent sunburn
- if used as directed with other sun protection measures (see Directions), decreases the risk of skin cancer and early skin aging caused by the sun.

WARNINGS

- For external use only
- Do not use on damaged or broken skin

Keep out of reach of children

When using this product keep out of eyes. Rinse with water to remove

Stop use and ask a doctor if rash occurs

DOSAGE AND ADMINISTRATION

- Applying liberally an evenly 15 minutes before sun exposure
- reapply at least every 2 hours
- use a water-resistant sunscreen if swimming or sweating
- Sun Protection Measures
- spending time in the sun increases your risk of skin cancer and early aging. To decrease this risk, regularly use a sunscreen with a Broad Spectrum SPF value of 15 or high and other sun protection measures including:
- limit time in the sun, especially from 10 am-2 pm
- wear long-sleeved shirts, pants, hats, and sunglasses
- children under 6 months age: Ask a doctor

OTHER SAFETY INFORMATION

Protect the product in this container from excessive heat and direct sun.

INACTIVE INGREDIENT

WATER

ETHYLHEXYL PALMITATE

ETHYLHEXYL STEARATE

BUTYLENE GLYCOL

BUTYLOCTYL SALICYLATE

CAPRYLYL TRISILOXANE

DIPHENYLSILOXY PHENYL TRIMETHICONE

POLYGLYCERYL-3 POLYDIMETHYLSILOXYETHYL DIMETHICONE (4000 MPA.S)

ALKYL (C12-15) BENZOATE

DICAPRYLYL CARBONATE

LIMONIA ACIDISSIMA BARK

ZANTHOXYLUM PIPERITUM FRUIT PULP

GREEN TEA LEAF

YEAST, UNSPECIFIED

HOUTTUYNIA CORDATA TOP

TANACETUM COCCINEUM FLOWER

NYMPHAEA ALBA FLOWER

CORYMBIA CITRIODORA LEAF OIL

POLYGLYCERYL-2 DIPOLYHYDROXYSTEARATE

POLYHYDROXYSTEARIC ACID STEARATE

POLYMETHYLSILSESQUIOXANE (11 MICRONS)

SODIUM CHLORIDE

VINYL DIMETHICONE/METHICONE SILSESQUIOXANE CROSSPOLYMER

SILICON DIOXIDE

DISTEARDIMONIUM HECTORITE

TRIETHOXYCAPRYLYLSILANE

CAPRYLYL GLYCOL

GLYCERYL CAPRYLATE

DIMETHICONE

ALLANTOIN

TOCOPHEROL

DIPROPYLENE GLYCOL

SODIUM PALMITOYL PROLINE

DISODIUM EDTA-COPPER